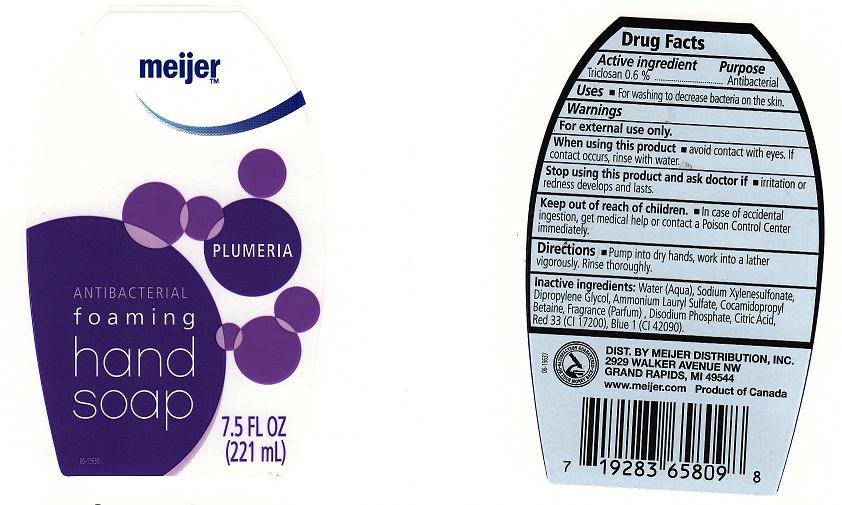 DRUG LABEL: ANTIBACTERIAL FOAMING
NDC: 41250-173 | Form: SOAP
Manufacturer: MEIJER
Category: otc | Type: HUMAN OTC DRUG LABEL
Date: 20100720

ACTIVE INGREDIENTS: TRICLOSAN 0.6000 mL/100 mL

DRUG FACTS BOX (BACK LABEL)

ACTIVE INGREDIENT

TRICLOSAN 0.6% (ANTIBACTERIAL)

USES AND DIRECTIONS

- USES: FOR WASHING TO DECREASE BACTERIA ON THE SKIN.

- DIRECTIONS: PUMP INTO DRY HANDS,WORK INTO A LATHER VIGOROUSLY. RINSE THOROUGHLY.

WARNINGS

FOR EXTERNAL USE ONLY.

WHEN USING THIS PRODUCT

AVOID CONTACT WITH EYES. IF CONTACT OCCURS, RINSE WITH WATER.

STOP USING THIS PRODUCT AND ASK DOCTOR IF

IRRITATION OR REDNESS DEVELOPS AND LASTS.

KEEP OUT OF REACH OF CHILDREN

IN CASE OF ACCIDENTAL INGESTION, GET MEDICAL HELP OR CONTACT A POISON CONTROL CENTER IMMEDIATELY.

PACKAGE FRONT AND BACK LABELS

7.5 OZ FRONT AND BACK LABELS: meijer8.jpg